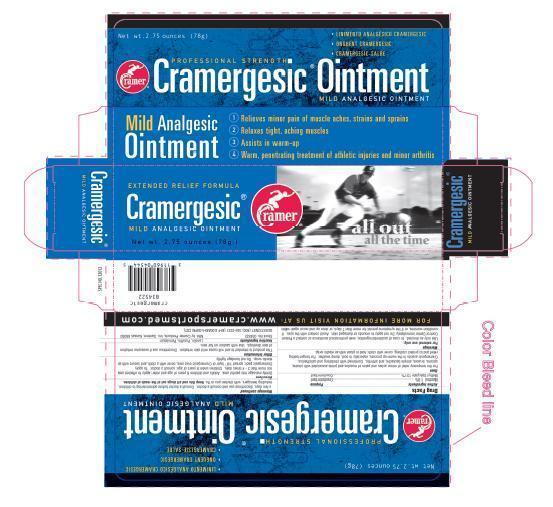 DRUG LABEL: Cramergesic
NDC: 11960-0045 | Form: OINTMENT
Manufacturer: Cramer Products Inc
Category: otc | Type: HUMAN OTC DRUG LABEL
Date: 20130419

ACTIVE INGREDIENTS: menthol 0.019 g/1 g; methyl salicylate 0.137 g/1 g
INACTIVE INGREDIENTS: lanolin; paraffin; petrolatum

Drug Facts

Active Ingredients Purpose

Menthol 1.9% Counterirritant

Methyl Salicylate 13.7% Counterirritant

Uses

For the temporary relief of minor aches and pains of muscles and joints associated with strain, sprains, bruises, simple backache, and arthritis. Combined with stretching and calisthenics, Cramergesic assists in the warm-up process, especially in cool, damp weather. For longer-lasting relief and to protect clothing, cover with cloth; hold in place with an elastic wrap.

Warnings

For external use only.
Use only as directed. In case of accidental ingestion, seek professional assistance or contact a Poison Control Center immediately. Do not apply to wounds or damaged skin. Avoid contact with the eyes. If condition worsens, or if the symptoms persist for more than 7 days, or clear up and occur again within a few days, discontinue use and consult a doctor. Consult a doctor before administering to children, including teenagers, with chicken pox or flu.

Directions

Gently massage into painful area. Adults and children 6 years of age and older: apply to affected area not more than 3 - 4 times daily. Children under 6 years of age: consult a doctor. To apply Cramergesic pack: spread 1/8 " layer of Cramergesic over area, cover with a cloth, and secure with an elastic wrap. Do not bandage tightly.

Other information

This product is intended to and will cause mild skin irritation. Discontinue use if excessive irritation of skin develops. Use with caution on fair skin.

Inactive Ingredients

Lanolin, Paraffin, Petrolatum

QUESTIONS

Stock No. 034522 Mfd. by Cramer Products, Inc. Gardner, Kansas 66030

QUESTIONS? (800) 345-2231 (M-F 8:00AM-5:00PM CST)

FOR MORE INFORMATION VISIT US AT WWW.CRAMERSPORTSMED.COM

PRINCIPAL DISPLAY PANEL

Net wt.2.75 ounces (78g)
PROFESSIONAL STRENGTH
CRAMERGESIC OINTMENT
MILD ANALGESIC OINTMENT

1. Relieves minor pain of muscle aches, strains and sprains
2. Relaxes tight, aching muscles
3. Assists in warm-up
4. Warm, penetrating treatment of athletic injuries and minor arthritis

Purpose

counterirritant

KEEP OUT OF REACH OF CHILDREN

Keep this and all drugs out of the reach of children.